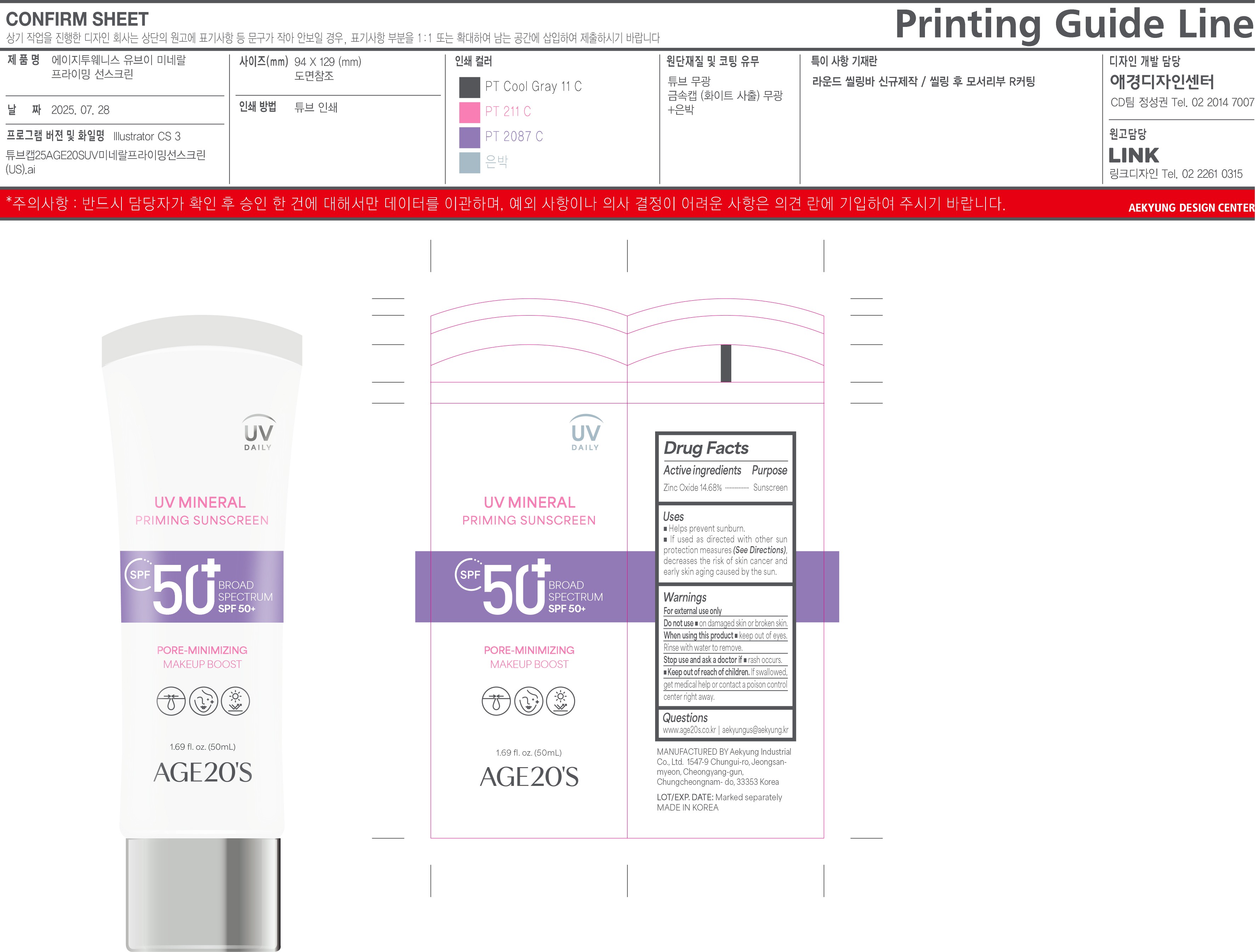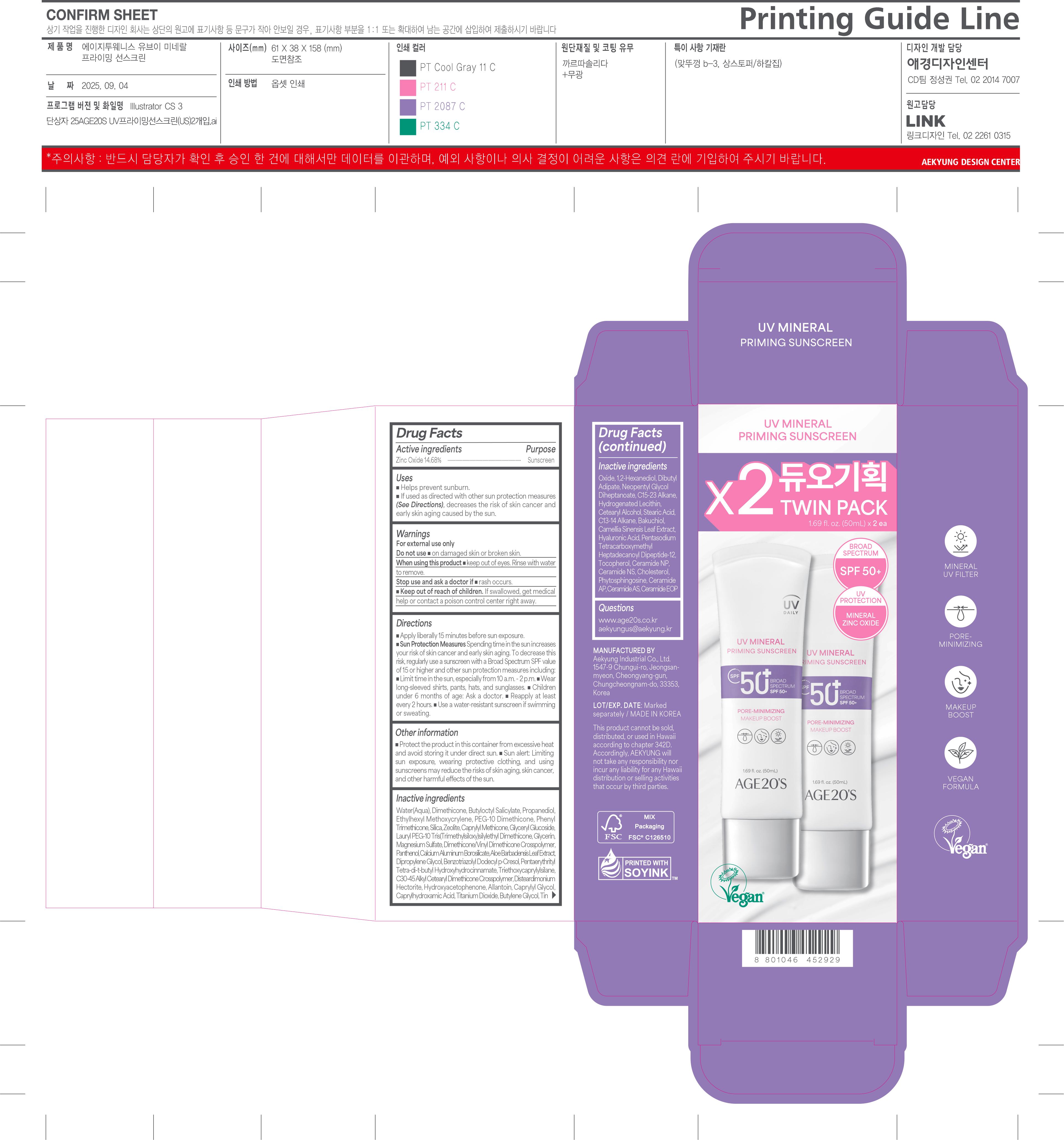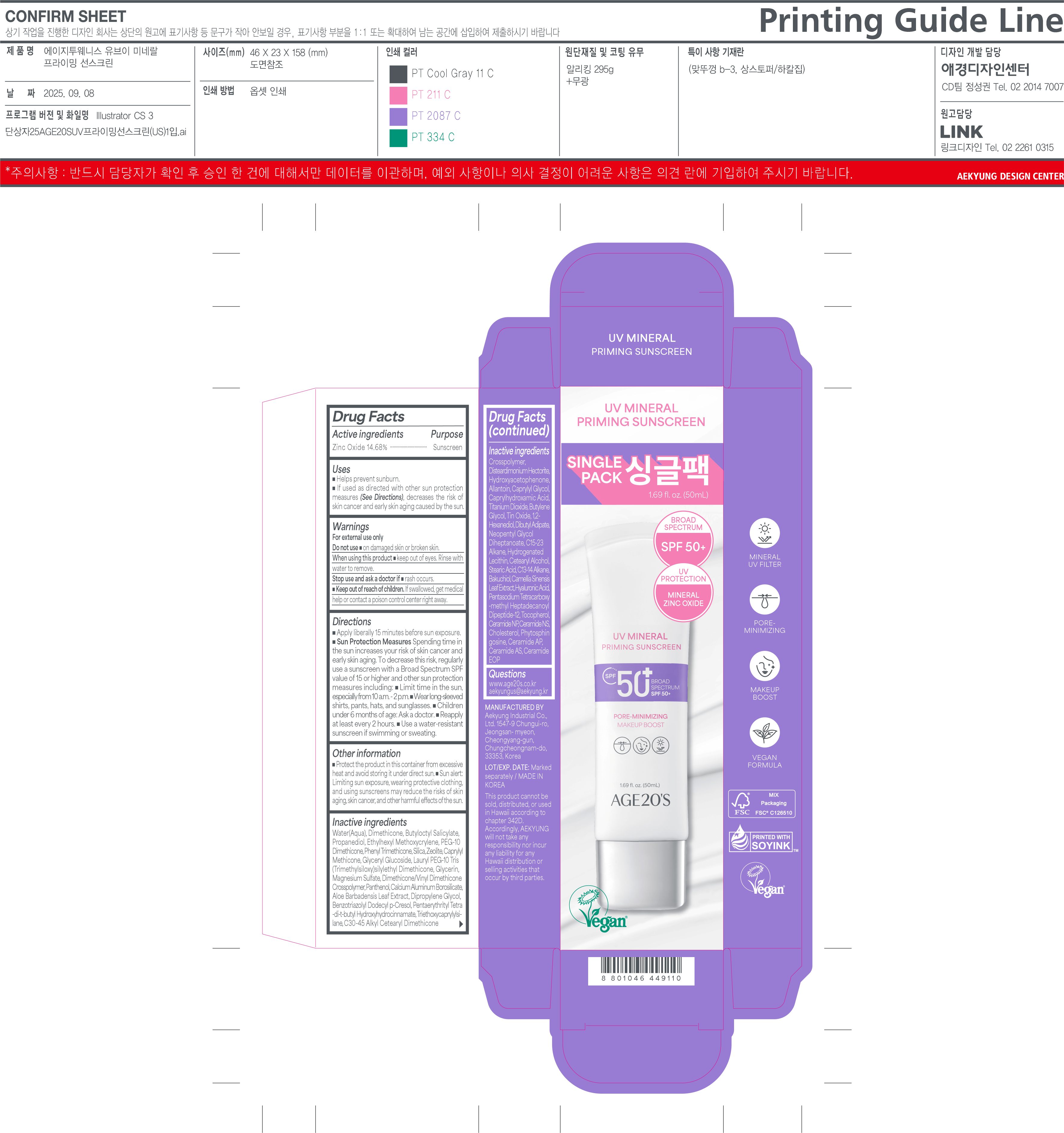 DRUG LABEL: AGE20S UV MINERAL PRIMING SUNSCREEN
NDC: 67225-5301 | Form: CREAM
Manufacturer: Aekyung Industrial Co., Ltd.
Category: otc | Type: HUMAN OTC DRUG LABEL
Date: 20251117

ACTIVE INGREDIENTS: ZINC OXIDE 7.34 g/50 g
INACTIVE INGREDIENTS: WATER; TRIETHOXYCAPRYLYLSILANE; HYDROXYACETOPHENONE; CERAMIDE NP; CERAMIDE NS; PHENYL TRIMETHICONE; DIPROPYLENE GLYCOL; BUTYLENE GLYCOL; ALLANTOIN; DISTEARDIMONIUM HECTORITE; PHYTOSPHINGOSINE; TITANIUM DIOXIDE; 1,2-HEXANEDIOL; NEOPENTYL GLYCOL DIHEPTANOATE; CERAMIDE 9; TIN OXIDE; ALOE BARBADENSIS LEAF; C30-45 ALKYL CETEARYL DIMETHICONE CROSSPOLYMER; PROPANEDIOL; ZEOLITE A; GLYCERYL GLUCOSIDE; GLYCERIN; PANTHENOL; CAPRYLHYDROXAMIC ACID; DIBUTYL ADIPATE; CHOLESTEROL; HYALURONIC ACID; DIMETHICONE; DIMETHICONE/VINYL DIMETHICONE CROSSPOLYMER (SOFT PARTICLE); PEG-10 DIMETHICONE (300 CST); C13-14 ISOPARAFFIN; PENTAERYTHRITYL TETRA-DI-T-BUTYL HYDROXYHYDROCINNAMATE; CETEARYL ALCOHOL; STEARIC ACID; BUTYLOCTYL SALICYLATE; SILICA; CAPRYLYL METHICONE; BAKUCHIOL; MAGNESIUM SULFATE; BENZOTRIAZOLYL DODECYL P-CRESOL; C15-23 ALKANE; HYDROGENATED SOYBEAN LECITHIN; TOCOPHEROL; CAPRYLYL GLYCOL; ETHYLHEXYL METHOXYCRYLENE; CERAMIDE AP; CALCIUM ALUMINUM BOROSILICATE

67225-5301 AGE20S UV MINERAL PRIMING SUNSCREEN

ACTIVE INGREDIENT

Zink Oxide 14.68%

Sunscreen

INDICATIONS AND USAGE

■ Helps prevent sunburn.

■ If used as directed with other sun protection measures (See Directions), decreases the risk of skin cancer and early skin aging caused by the sun.

WARNINGS

For external use only

DO NOT USE

■ on damaged skin or broken skin

WHEN USING

■ keep out of eyes. Rinse with water to remove.

stop use and ask a doctor if ■ rash occurs.

KEEP OUT OF REACH OF CHILDREN

If swallowed, get medical help or contact poison control center right away

INACTIVE INGREDIENT

Water

Dimethicone
Butyloctyl Salicylate
Propanediol
Ethylhexyl Methoxycrylene
PEG-10 Dimethicone
Phenyl Trimethicone
Silica
Zeolite
Caprylyl Methicone
Glyceryl Glucoside
Lauryl PEG-10 Tris(Trimethylsiloxy)silylethyl Dimethicone
Glycerin
Magnesium Sulfate
Dimethicone/Vinyl Dimethicone Crosspolymer
Panthenol
Calcium Aluminum Borosilicate
Aloe Barbadensis Leaf Extract
Dipropylene Glycol
Benzotriazolyl Dodecyl p-Cresol
Pentaerythrityl Tetra-di-t-butyl Hydroxyhydrocinnamate
Triethoxycaprylylsilane
C30-45 Alkyl Cetearyl Dimethicone Crosspolymer
Disteardimonium Hectorite
Hydroxyacetophenone
Allantoin
Caprylyl Glycol
Caprylhydroxamic Acid
Titanium Dioxide
Butylene Glycol
Tin Oxide
1,2-Hexanediol
Dibutyl Adipate
Neopentyl Glycol Diheptanoate
C15-23 Alkane
Hydrogenated Lecithin
Cetearyl Alcohol
Stearic Acid
C13-14 Alkane
Bakuchiol
Camellia Sinensis Leaf Extract
Hyaluronic Acid
Pentasodium Tetracarboxymethyl Heptadecanoyl Dipeptide-12
Tocopherol
Ceramide NP
Ceramide NS
Cholesterol
Phytosphingosine
Ceramide AP
Ceramide AS
Ceramide EOP

DOSAGE AND ADMINISTRATION

■ Apply liberally 15 minutes before sun exposure.
■ Sun Protection Measures. Spending time in the sun increases your risk of skin cancer and early skin aging. Todecrease this risk, regularly use a sunscreen with a Broad Spectrum SPF value of 15 or higher and other sun protection measures including:

■ Children under 6 months of age: Ask a doctor.

■ Reapply at least every 2 hours.

■ Use a water-resistant sunscreen if swimming or sweating

■ Limit time in the sun, especially from 10 a.m. - 2 p.m.

■ Wear long-sleeved shirts, pants, hats, and sunglasses

OTHER SAFETY INFORMATION

■ Protect the product in the container from excessive heat and avoid storing it under direct sun.

■ Sun alert: Limiting sun exposure, wearing protective clothing, and using sunscreens may reduce the risks of skin aging, skin cancer, and other harmful effects of the sun.